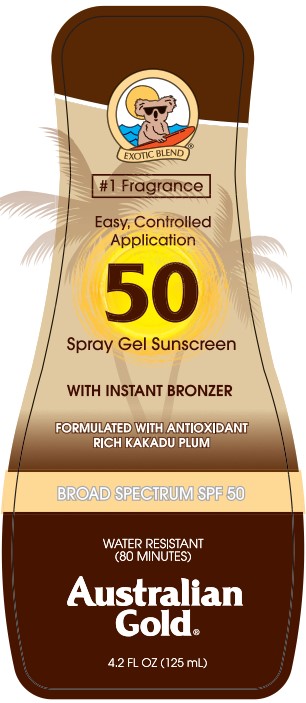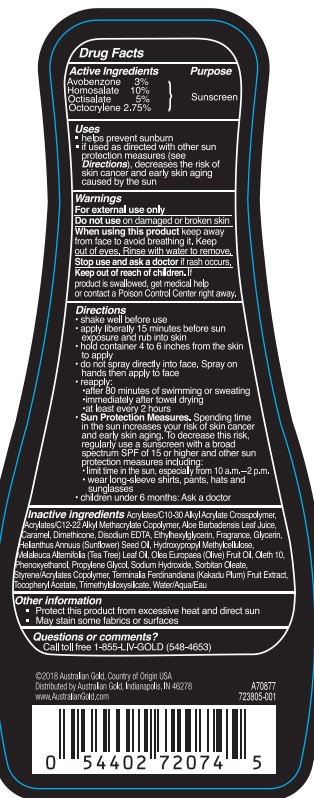 DRUG LABEL: Australian Gold
NDC: 58443-0578 | Form: SPRAY
Manufacturer: Prime Enterprises Inc.
Category: otc | Type: HUMAN OTC DRUG LABEL
Date: 20221109

ACTIVE INGREDIENTS: AVOBENZONE 29.04 g/1 mL; HOMOSALATE 96.8 g/1 mL; OCTISALATE 48.4 g/1 mL; OCTOCRYLENE 26.62 g/1 mL
INACTIVE INGREDIENTS: WATER; SUNFLOWER OIL; TEA TREE OIL; OLIVE OIL; PHENOXYETHANOL; SORBITAN MONOOLEATE; ETHYLHEXYLGLYCERIN; KAKADU PLUM; .ALPHA.-TOCOPHEROL ACETATE; TRIMETHYLSILOXYSILICATE (M/Q 1.0-1.2); CARBOMER INTERPOLYMER TYPE A (55000 CPS); BUTYL ACRYLATE/C16-C20 ALKYL METHACRYLATE/METHACRYLIC ACID/METHYL METHACRYLATE COPOLYMER; DIMETHICONE; HYPROMELLOSES; PROPYLENE GLYCOL; ALOE VERA LEAF; GLYCERIN; SODIUM HYDROXIDE; CARAMEL; STYRENE/ACRYLAMIDE COPOLYMER (MW 500000); EDETATE DISODIUM ANHYDROUS; OLETH-10

Australian Gold Instant Bronzer 50 Spray Gel Sunscreen

Active Ingredients

Avobenzone 3%

Homosalate 10%

Octisalate 5%

Octocrylene 2.75%

Purpose

Sunscreen

Uses

- helps prevent sunburn • if used as directed with other sun protection measures (see Directions), decreases the risk of skin cancer and early skin aging caused by the sun

Warnings

For external use only

Do not use on damaged or broken skin

When using this product keep away from face to avoid breathing it. Keep out of eyes.

Rinse with water to remove.

Stop use and ask a doctor if rash occurs

Keep out of reach of children. If product is swallowed, get medical help or contact a Poison Control Center right away.

Directions

- shake well before use • apply liberally 15 minutes before sun exposure and rub into skin • hold container 4 to 6 inches from the skin to apply • do not spray directly into face. Spray on hands then apply to face • reapply: • after 80 minutes of swimming or sweating • immediately after towel drying • at least every 2 hours • Sun Protection Measures. Spending time in the sun increases your risk of skin cancer and early skin aging. To decrease this risk regularly use a sunscreen with a broad spectrum SPF of 15 or higher and other sun protection measures including: • limit time in the sun, especially from 10 a.m. – 2 p.m. • wear long-sleeve shirts, pants, hats, and sunglasses • children under 6 months: Ask a doctor

Inactive ingredients

Acrylates/C10-30 Alkyl Acrylate Crosspolymer, Acrylates/C12-22 Alkyl Methacrylate Copolymer, Aloe Barbadensis Leaf Juice, Caramel, Dimethicone, Disodium EDTA, Ethylhexylglycerin, Fragrance, Glycerin, Helianthus Annuus (Sunflower) Seed Oil, Hydroxypropyl Methylcellulose, Melaleuca Alternifolia (Tea Tree) Leaf Oil, Olea Europaea (Olive) Fruit Oil, Oleth 10, Phenoxyethanol, Propylene Glycol, Sodium Hydroxide, Sorbitan Oleate, Styrene/Acrylates Copolymer, Terminalia Ferdinandiana (Kakadu Plum) Fruit Extract, Tocopheryl Acetate, Trimethylsiloxysilicate, Water

Other information

- Protect this product from excessive heat and direct sun
- May stain some fabrics or surfaces

Questions or comments?

Call toll free 1-855-LIV-GOLD (548-4653)